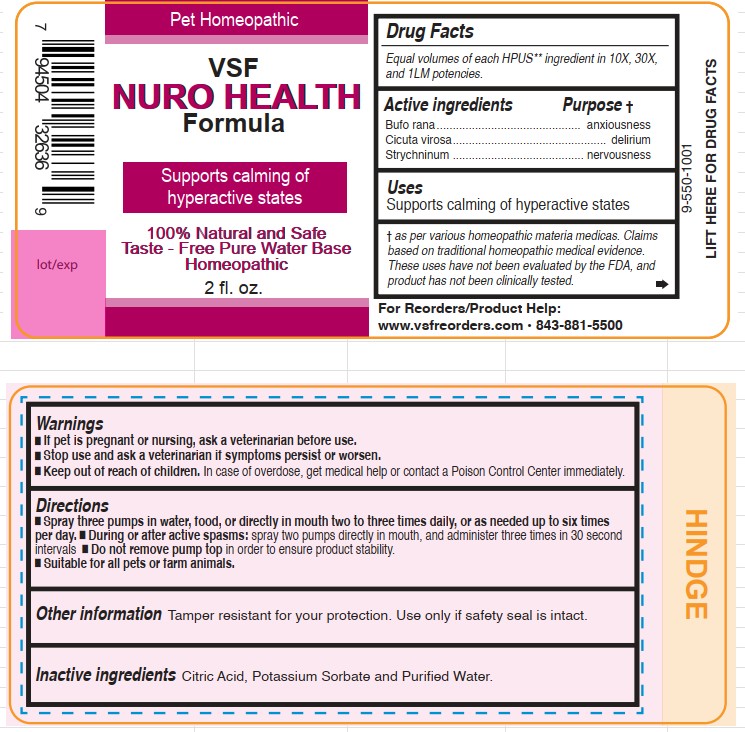 DRUG LABEL: Nuro Health Formula
NDC: 86100-0011 | Form: LIQUID
Manufacturer: Vsf2 Inc.
Category: homeopathic | Type: OTC ANIMAL DRUG LABEL
Date: 20250723

ACTIVE INGREDIENTS: BUFO BUFO CUTANEOUS GLAND 10 [hp_X]/59 mL; CICUTA VIROSA ROOT 10 [hp_X]/59 mL; STRYCHNINE 10 [hp_X]/59 mL
INACTIVE INGREDIENTS: ANHYDROUS CITRIC ACID; POTASSIUM SORBATE; WATER

VSFNuro Health Formula

Active ingredients

Equal volumes of each HPUS** ingredient in 10X,
30X, and 1LM potencies.

Bufo rana, Cicuta virosa, and Strychninum.

As per various homeopathic materia medicas. Claims based on traditional homeopathic medical evidence.

These uses have not been evaluated by the FDA, and product has not been clinically tested.

Uses

Supports calming of hyperactive states.

Questions

VSF Nuro Health Formula 2Fl. oz.

Pet Homeopathic

100% Natural and Safe Taste

Free Pure Water Base

For Reorders/Product Help:

www.vsfreorders.com 843-881-5500

Warmings

- If pet is pregnant or nursing, ask a veterinarian before use.
- Stop use and ask a veterinarian if symptoms persist or worsen.
- Keep out of reach of children. In case of overdose, get medical help or contact a Poison Control Center immediately.

Keep out of reach of children.

In case of overdose, get medical help or contact a Poison Control Center immediately.

Directions

- Spray three pumps in water, food, or directly in mouth two to three times daily, or as needed up to six times per day.
- During or after active spasms: spray two pumps directly in mouth, and administer three times in 30 second intervals.
- Do not remove pump top in order to ensure product stability.
- Suitable for all pets or farm animals.

Other information

Tamper resistant for your protection.

Use only if safety seal is intact.

Inactive Ingredients

Citric Acid, Potassium Sorbate, and Purified Water.

Active Ingredients Purpose †

Bufo rana....................................anxiousness

Cicuta virosa....................................delirium

Strychninum...............................nervousness

As per various homeopathic materia medicas. Claims based on traditional homeopathic medical evidence.

These uses have not been evaluated by the FDA, and product has not been clinically tested.